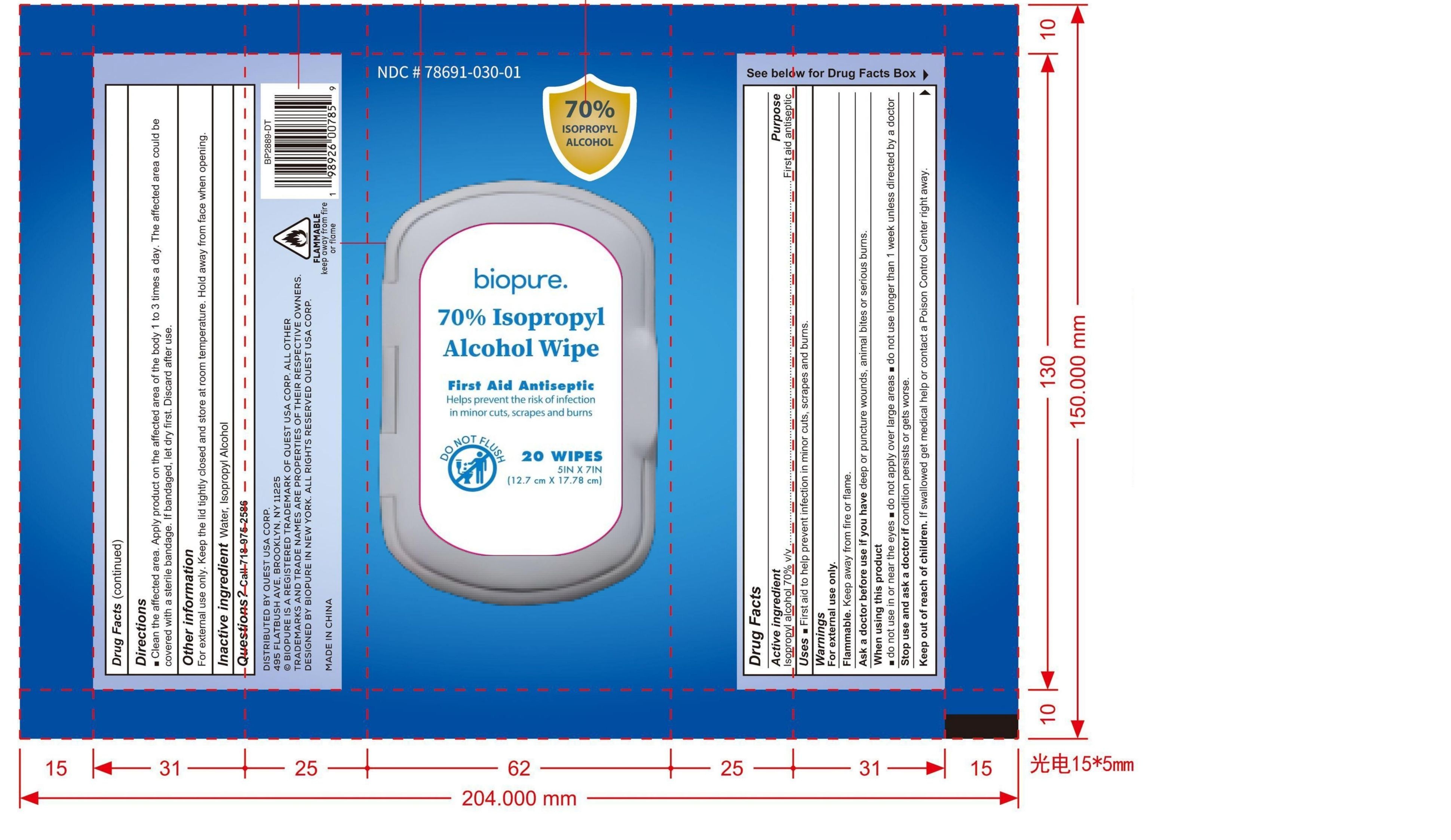 DRUG LABEL: Biopure 70% Isopropyl Alcohol Wipe
NDC: 78691-030 | Form: CLOTH
Manufacturer: QUEST USA CORP
Category: otc | Type: HUMAN OTC DRUG LABEL
Date: 20250721

ACTIVE INGREDIENTS: ISOPROPYL ALCOHOL 2.7 mL/1 1
INACTIVE INGREDIENTS: WATER

BIOPURE 70% Isopropyl Alcohol Wipe

Active ingredient

Isopropyl Alcohol 70% v/v

Purpose

First aid antiseptic

Uses

First aid to help prevent infection in minor cuts, scrapes, and burns.

Warnings

For external use only. Flammable. Keep away from heat or flame.

Ask a doctor before use if you have deep or puncture wounds, animal bites or serious burns.

Keep out of reach of children. If swallowed, get medical help or contact a Poison Control Center right away.

Stop use and ask a doctor if condition persists or gets worse.

- do not use in or near the eyes
- do not apply over large areas
- do not use longer than 1 week unless directed by a doctor.

Directions

- Clean the affected area. Apply product on the affected area of the body 1 to 3 times a day. The affected area could be covered with a sterile bandage. If bandaged, let dry first. Discard after use.

Other information

For external use only. Keep the lid tightly closed and store at room temperature. Hold away from face when opening.

Inactive ingredients

Water

Questions?

Call 718-975-2586